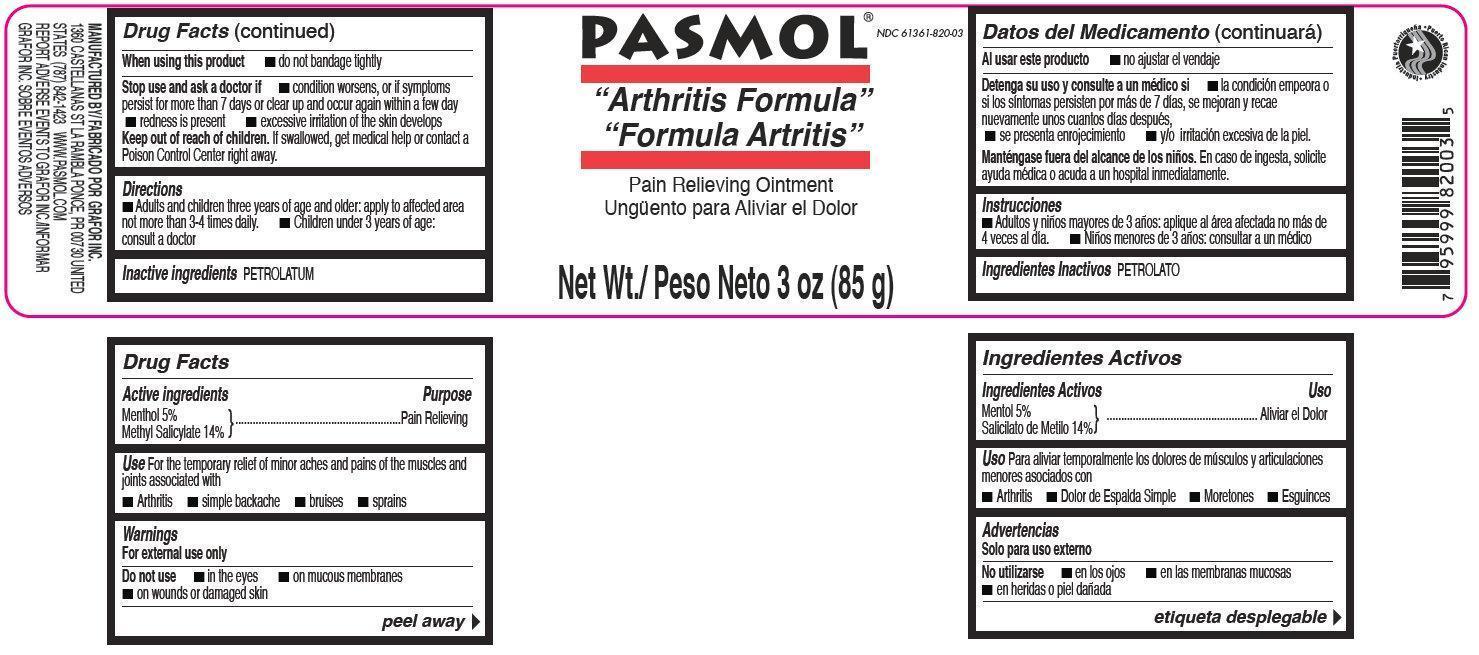 DRUG LABEL: Pasmol Pain Relieving
NDC: 61361-820 | Form: CREAM
Manufacturer: Grafor, Inc.
Category: otc | Type: HUMAN OTC DRUG LABEL
Date: 20150408

ACTIVE INGREDIENTS: MENTHOL 5 g/100 g; METHYL SALICYLATE 14 g/100 g
INACTIVE INGREDIENTS: PETROLATUM

Pasmol Pain Relieving Ointment

Active ingredients

Menthol 5%

Methyl Salicylate 14%

Purpose

Pain Relieving

Uses

For the temporary relief of minor aches and pains of the muscles and joints associated with:

- Arthritis
- simple backache
- bruises
- sprains

Warnings

For external use only.

Do not use

- in the eyes
- on mucous membranes
- on wounds or damaged skin

When using this product

- do not bandage tightly

Stop use and ask a doctor if

- condition worsens or symptoms persist for more than 7 days or clear up and occur again within a few day
- redness is present
- excessive irritation of the skin develops

Keep out of reach of children

If swallowed, get medical help or contact a Poison Control Center right away.

Directions

- Adults and children three years of age and older: apply to affected area not more than 3-4 times daily.
- Children under 3 years of age: consult a doctor

Inactive ingredients

PETROLATUM

MANUFACTURED BY GRAFOR INC. 1360 CASTELLANAS ST LA RAMBLA PONCE, PR 00730 UNITED STATES (787) 842-1423 WWW.PASMOL.COM REPORT ADVERSE EVENTS TO GRAFOR INC.

Pasmol Pain Relieving Ointment, 85g (61361-820-03)

PASMOL

“Arthritis Formula”

“Formula Artritis”

Pain Relieving Ointment

Net Wt./ Peso Neto 3 oz (85 g)